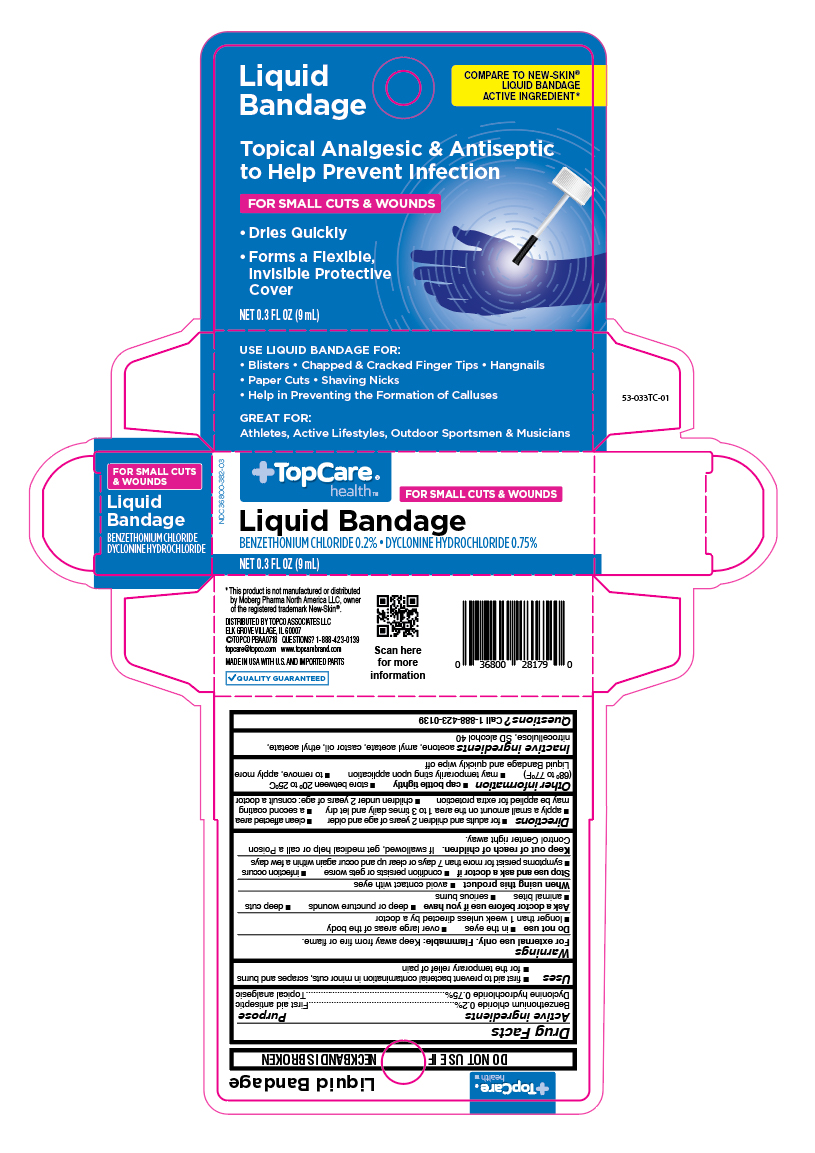 DRUG LABEL: Benzethonium chloride Plus Dyclonine hydrochloride
NDC: 36800-382 | Form: LIQUID
Manufacturer: Topco Associates LLC
Category: otc | Type: HUMAN OTC DRUG LABEL
Date: 20251007

ACTIVE INGREDIENTS: BENZETHONIUM CHLORIDE 0.2 mg/9 mL; DYCLONINE HYDROCHLORIDE 0.75 mg/9 mL
INACTIVE INGREDIENTS: ACETONE; AMYL ACETATE; CASTOR OIL; ETHYL ACETATE; PYROXYLIN; ALCOHOL

TopCare Liquid Bandage

Active ingredients

Benzethonium chloride 0.2%

Dyclonine hydrochloride 0.75%

Purpose

First aid antiseptic

Topical analgesic

Uses

- first aid to prevent bacteria contamination in minor cuts and scrapes

Warnings

For external use only.

Flammable:

do not use while smoking or near heat or flame.

Do not use

- in the eyes
- over large areas of the body
- longer than 1 week unless directed by a doctor
- on infected areas or wounds that are draining
- with other first aid products such as lotions and creams
- over sutures
- on mucous membranes

Ask a doctor before use if you have

- deep puncture wounds
- deep cuts
- animal bites
- serious bleeding
- diabetes
- poor circulation
- serious burns

When using this product

- do not sotre at temperaure above 120oF

Intentional misuse by deliberately concentrating and inhaling the contents can be harmful or fatal.

Stop use and ask a doctor if

- conditions persists or gets worse
- infection occurs

Keep out of reach of children.

If swallowed, get medical help or call a Poison Control Center right away.

Directions

- Clean affected area
- apply a small amount on the area 1-3 times daily
- let dry
- a second coating may be applied for extra protection
- to remove, apply more Liquid Bandage and quickly wipe off
- finger nail polish remover may dissolve Liquid Bandage

Other information

- cap bottle tightly
- store at room temperature away from heat
- may temporarily sting upon application
- do not allow to come in contact with floors, countertops, or other finished surfaces - will stain

Inactive ingredients

acetone, amyl acetate, castor oil, ethyl acetate, nitrocellulose, SD slcohol 40

Questions

Call 1-866-964-0939

Principal Display Panel

TopCare

Liquid

Bandage

Topical Analgesic & Antiseptic to Help Prevent Infection

FOR SMALL CUTS & WOUNDS

- Dries Quickly
- Forms a Flexible, Invisible Protective Cover

USE LIQUID BANDAGE FOR:

- Blisters
- Chapped & Cracked Finger Tips
- Hangnails
- Paper Cuts
- Shaving Nicks
- Help in Preventing the Formulation of Calluses

GREAT FOR:

Athletes, Active Lifestyles, Outdoor Sportmen & Musicians

NET 0.3 FL OZ (9 mL)